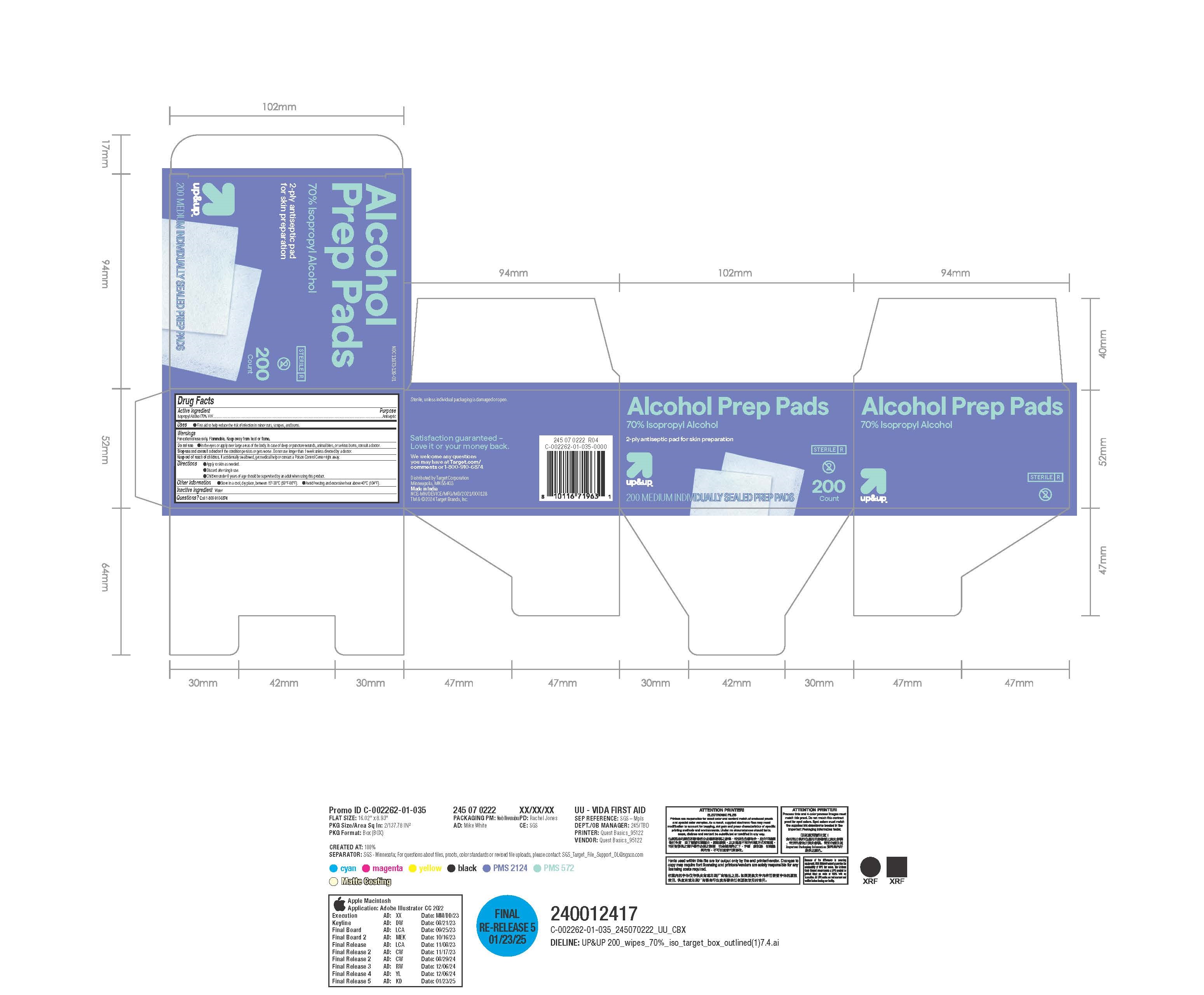 DRUG LABEL: Alcohol prep pad
NDC: 11673-139 | Form: CLOTH
Manufacturer: Target Corporation
Category: otc | Type: HUMAN OTC DRUG LABEL
Date: 20250219

ACTIVE INGREDIENTS: ISOPROPYL ALCOHOL 70 g/100 1
INACTIVE INGREDIENTS: WATER

Up&Up Alcohol Prep Pads

Active Ingredient(s)

Isopropyl Alcohol 70%

Purpose

Antiseptic

Use

First aid to help reduce the risk of infection in minor cuts, scrapes, and burns.

Warnings

For external use only.Flammable.Keep away from heat or flame.

Do not use
in the eyes or apply over large areas of the body.In case of deep or puncture wounds, animal bites, or serious burns, consulta doctor.

Stop use and consulta doctor if the condition persists or gets worse.Do not use longer than 1 week unless directed by a doctor.

Keep out of reach of children.If accidentally swallowed, get medical help or contact a Poison Control Center right away.

Do not use

in the eyes or apply over large areas of the body.In case of deep or puncture wounds, animal bites, or serious burns, consulta doctor.

Do not use
in the eyes or apply over large areas of the body.In case of deep or puncture wounds, animal bites, or serious burns, consulta doctor.

Stop use and consulta doctor if the condition persists or gets worse.Do not use longer than 1 week unless directed by a doctor.

Keep out of reach of children.If accidentally swallowed, get medical help or contact a Poison Control Center right away.

Stop use and consulta doctor if the condition persists or gets worse.Do not use longer than 1 week unless directed by a doctor.

Keep out of reach of children.If accidentally swallowed, get medical help or contact a Poison Control Center right away.

Directions

Apply to skin as needed.
●Discard after single use.
●Children under 6 years of age should be supervised by an adult when using this product.

Other information

Store in a cool, dry place, between 15°-30°C(59°F-86°F) .
Avoid freezing and excessive heat above 40°C(104°F) .

Inactive ingredients

Water

Package Label - Principal Display Panel

200 Pads in 1 BOX